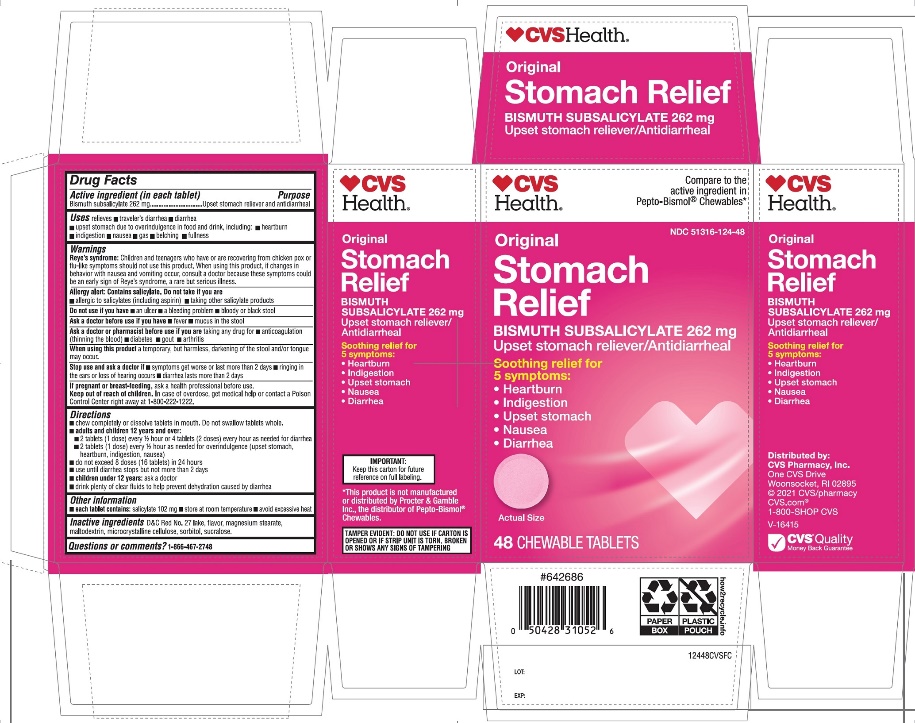 DRUG LABEL: CVS Stomach Relief
NDC: 51316-124 | Form: TABLET
Manufacturer: CVS
Category: otc | Type: HUMAN OTC DRUG LABEL
Date: 20251208

ACTIVE INGREDIENTS: BISMUTH SUBSALICYLATE 262 mg/1 1
INACTIVE INGREDIENTS: D&C RED NO. 27; MAGNESIUM STEARATE; MALTODEXTRIN; MICROCRYSTALLINE CELLULOSE; SORBITOL; SUCRALOSE

CVS Digestive Relief 48 Chewable Tablets Drug Facts

Drug Facts

Active ingredient (in each tablet)

Bismuth subsalicylate 262 mg

Purpose

Upset stomach reliever and anti-diarrheal

Uses

relieves

- traveler’s diarrhea
- diarrhea
- upset stomach due to overindulgence in food and drink including
- heartburn
- indigestion
- nausea
- gas
- belching
- fullness

Warnings

Reye's syndrome

Children and teenagers who have or are recovering from chicken pox or flu-like symptoms should not use this product. When using this product, if changes in behavior with nausea and vomiting occur, consult a doctor because these symptoms could be an early sign of Reye's syndrome, a rare but serious illness.

Allergy alert:

Contains salicylate. Do not take if you are

- allergic to salicylates (including aspirin)
- taking other salicylate products

Do not use ifyou have

- bloody or black stool
- an ulcer
- a bleeding problem

Ask a doctor before use if you have

- fever
- mucus in the stool

Ask a doctor before use if you are taking any drug for

- anticoagulation (thinning of the blood)
- diabetes
- gout
- arthritis

WHEN USING

When using this producta temporary, but harmless, darkening of the stool and/or tongue may occur.

Stop use and ask a doctor if

- symptoms get worse or last more than 2 days
- ringing in the ears occurs or loss of hearing occurs
- diarrhea lasts more than 2 days

PREGNANCY OR BREAST FEEDING

If pregnant or breast feeding,ask a health professional before use.

Keep out of reach of children. In case of overdose, get medical help or contact a Poison Control Center immediately.1-800-222-1222.

Directions

- chew or dissolve tablets in mouth. Do not swallow tablets whole.
- adults and children 12 years and older:2 tablets (1 dose) every 1/2 hour or 4 tablets (2 dose) every hour as needed for diarrhea
- 2 tablets (1 dose) every 1/2 hour as needed for overindulgence (upset stomach, heartburn, indigestion, nausea)
- do not exceed 8 doses (16 tablets) in 24 hours
- use until diarrhea stops but not more than 2 days
- children under 12 years:ask a doctor
- drink plenty of clear fluids to help prevent dehydration caused by diarrhea

Other information

- each tablets contains:salicylate 102 mg
- store at room temperature
- avoid excessive heat

Inactive ingredients

D&C Red# 27 lake, flavor, magnesium stearate, maltodextrin, microcrystalline cellulose, sorbitol, sucralose.

Questions or comments?

1-866-467-2748

PRINCIPAL DISPLAY PANEL

NDC 51316-124-48

Compare toactive ingredient in Pepto-Bismol® Chewables*

Stomach Relief

Chewable tablets

Bismuth subsalicylate, Upset Stomach Reliever / Antidiarrheal

5- symptom digestive relief

- Upset stomach,
- Nausea,
- Heartburn,
- Indigestion,
- Diarrhea
- Original flavor

48 chewable tablets

TAMPER EVIDENT: DO NOT USE IF CARTON IS OPENED OR IF STRIP UNIT IS TORN, BROKEN OR SHOWS ANY SIGNS OF TAMPERING

Dist.by

*This product is not manufactured or distributed by Procter & Gamble Inc., the distributor of PEPTO-BISMOL® Chewables.